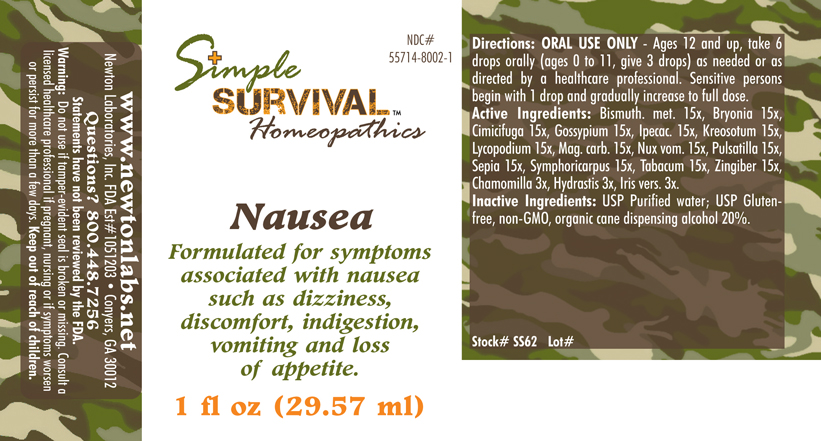 DRUG LABEL: Nausea 
NDC: 55714-8002 | Form: LIQUID
Manufacturer: Newton Laboratories, Inc.
Category: homeopathic | Type: HUMAN OTC DRUG LABEL
Date: 20140415

ACTIVE INGREDIENTS: Bismuth 15 [hp_X]/1 mL; Bryonia Alba Root 15 [hp_X]/1 mL; Black Cohosh 15 [hp_X]/1 mL; Gossypium Herbaceum Root Bark 15 [hp_X]/1 mL; Ipecac 15 [hp_X]/1 mL; Wood Creosote 15 [hp_X]/1 mL; Lycopodium Clavatum Spore 15 [hp_X]/1 mL; Magnesium Carbonate 15 [hp_X]/1 mL; Strychnos Nux-vomica Seed 15 [hp_X]/1 mL; Pulsatilla Vulgaris 15 [hp_X]/1 mL; Sepia Officinalis Juice 15 [hp_X]/1 mL; Symphoricarpos Albus Fruit 15 [hp_X]/1 mL; Tobacco Leaf 15 [hp_X]/1 mL; Ginger 15 [hp_X]/1 mL; Matricaria Recutita 3 [hp_X]/1 mL; Goldenseal 3 [hp_X]/1 mL; Iris Versicolor Root 3 [hp_X]/1 mL
INACTIVE INGREDIENTS: Alcohol

Nausea

INDICATIONS & USAGE SECTION

Nausea Formulated for symptoms associated with nausea such as dizziness, discomfort, indigestion, vomiting and loss of appetite.

DOSAGE & ADMINISTRATION SECTION

Directions: ORAL USE ONLY - Ages 12 and up, take 6 drops orally (ages 0 to 11, give 3 drops) as needed or as directed by a healthcare professional. Sensitive persons begin with 1 drop and gradually increase to full dose.

OTC - ACTIVE INGREDIENT SECTION

Bismuthum met. 15x, Bryonia 15x, Cimicifuga 15x, Gossypium 15x, Ipecac. 15x, Kreosotum 15x, Lycopodium 15x, Mag. carb. 15x, Nux vom. 15x, Pulsatilla 15x, Sepia 15x, Symphoricarpus 15x, Tabacum 15x, Zingiber 15x, Chamomilla 3x, Hydrastis 3x, Iris vers. 3x.

OTC - PURPOSE SECTION

Formulated for symptoms associated with nausea such as dizziness, discomfort, indigestion, vomiting and loss of appetite.

INACTIVE INGREDIENT SECTION

Inactive Ingredients: USP Purified Water; USP Gluten-free, non-GMO, organic cane dispensing alcohol 20%.

QUESTIONS SECTION

www.newtonlabs.net Newton Laboratories, Inc. FDA Est # 1051203 - Conyers, GA 30012
Questions? 1.800.448.7256

WARNINGS SECTION

Warning: Do not use if tamper - evident seal is broken or missing. Consult a licensed healthcare professional if pregnant, nursing or if symptoms worsen or persist for more than a few days. Keep out of reach of children.

OTC - PREGNANCY OR BREAST FEEDING SECTION

Consult a licensed healthcare professional if pregnant, nursing or if symptoms worsen or persist for more than a few days.

OTC - KEEP OUT OF REACH OF CHILDREN SECTION

Keep out of reach of children.